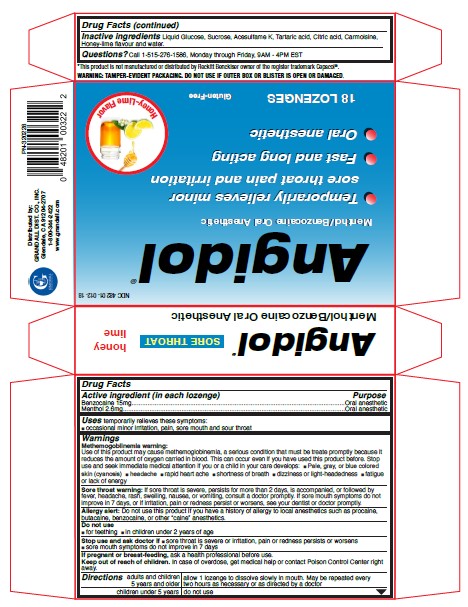 DRUG LABEL: Angidol
NDC: 48201-014 | Form: LOZENGE
Manufacturer: GRANDALL DISTRIBUTING, LLC
Category: otc | Type: HUMAN OTC DRUG LABEL
Date: 20240123

ACTIVE INGREDIENTS: BENZOCAINE 15 mg/1 1; MENTHOL 2.6 mg/1 1
INACTIVE INGREDIENTS: CARMOISINE; ANHYDROUS DEXTROSE; SUCROSE; WATER; ACESULFAME; TARTARIC ACID; ANHYDROUS CITRIC ACID

Grandall (as PLD) - Angidol Lozenges Honey-Lime Flavor (48201-014)

ACTIVE INGREDIENTS

BENZOCAINE 15MG

MENTHOL 2.6MG

PURPOSE

ORAL ANESTHETIC

USES

Temporarily relieves these symptoms:

- occasional minor irritation, pain, sore mouth and sore throat

Warnings

Methemogoblinemia warning:
Use of this product may cause methemoglobinemia, a serious condition that must be treate promptly because it reduces the amount of oxygen carried in blood. This can occur even if you have used this product before. Stop use and seek immediate medical attention if you or a child in your care develops:

- Pale, gray, or blue colored skin (cyanosis)
- headache
- rapid heart ache
- shortness of breath
- dizziness or light-headedness
- fatigue or lack of energy

Sore throat warning: If sore throat is severe, persists for more than 2 days, is accompanied, or followed by fever, headache, rash, swelling, nausea, or vomiting, consult a doctor promptly. If sore mouth symptoms do not improve in 7 days, or if irritation, pain or redness persist or worsens, see your dentist or doctor promptly. Allergy alert: Do not use this product if you have a history of allergy to local anesthetics such as procaine, butacaine, benzocaine, or other “caine” anesthetics.
Do not use

- for teething
- in children under 2 years of age

Stop use and ask doctor if

- sore throat is severe or irritation, pain or redness persists or worsens
- sore mouth symptoms do not improve in 7 days

If pregnant or breast-feeding, ask a health professional before use.

Keep out of reach of children. In case of overdose, get medical help or contact Poison Control Center right away.

Directions

adults and children 5 years and older: allow 1 lozenge to dissolve slowly in mouth. May be repeated every two hours as necessary or as directed by a doctor

children under 5 years: do not use

INACTIVE INGREDIENTS

HONEY-LIME FLAVOR: Liquid Glucose, Sucrose, Acesulfame K, Tartaric acid, Citric acid, Carmoisine, Honey-lime flavour and water.

Questions?

Call 1-515-276-1586, Monday through Friday, 9AM - 4PM EST